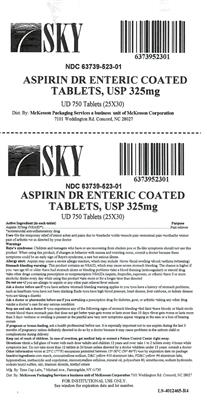 DRUG LABEL: Enteric Coated Aspirin
NDC: 63739-523 | Form: TABLET, DELAYED RELEASE
Manufacturer: McKesson Corporation dba SKY Packaging
Category: otc | Type: HUMAN OTC DRUG LABEL
Date: 20210120

ACTIVE INGREDIENTS: ASPIRIN 325 mg/325 1
INACTIVE INGREDIENTS: MODIFIED CORN STARCH (1-OCTENYL SUCCINIC ANHYDRIDE); CROSCARMELLOSE SODIUM; D&C YELLOW NO. 10; FD&C YELLOW NO. 6; METHACRYLIC ACID - ETHYL ACRYLATE COPOLYMER (1:1) TYPE A; MICROCRYSTALLINE CELLULOSE; MINERAL OIL; POLYSORBATE 80; DIMETHICONE; SILICON DIOXIDE; SODIUM HYDROXIDE; SODIUM LAURYL SULFATE; TALC; TITANIUM DIOXIDE; TRIETHYL CITRATE; HYPROMELLOSE, UNSPECIFIED

331R ASA DR ORANGE TABS 325 MG

Do not use

- if you are allergic to aspirin or any other pain reliever/fever reducer

Ask a doctor before use if

- stomach bleeding warning applies to you
- you have a history of stomach problems, such as heartburn
- you have high blood pressure, heart disease, liver cirrhosis, or kidney disease
- you are taking a diuretic
- you have asthma
- you have not been drinking fluids

Ask a doctor or pharmacist before use if you are

- taking a prescription drug for diabetes, gout, or arthritis
- taking any other drug
- under a doctor's care for any serious condition

Stop use and ask a doctor if

- you experience any of the following signs of stomach bleeding
-
  - feel faint
  - have bloody or black stools
  - vomit blood
  - have stomach pain that does not get better
- pain gets worse or lasts more than 10 days
- fever gets worse or lasts more than 3 days
- redness or swelling is present in the painful area
- any new symptoms appear
- ringing in the ears or a loss of hearing occurs

If pregnant or breast-feeding,

ask a health professional before use. It is especially important not to use aspirin during the last 3 months of pregnancy unless definitely directed to do so by a doctor because it may cause problems in the unborn child or complications during delivery.

Keep out of reach of children.

In case of overdose, get medical help or contact a Poison Control Center right away.

Directions

- drink a full glass of water with each dose
- adults and children 12 years and over: take 1 to 2 tablets every 4 hours while symptoms last. Do not take more than 12 tablets in 24 hours unless directed by a doctor
- children under 12 years: consult a doctor

Other information

- store at 25° C (77° F) excursions permitted between 15°-30° C (59°-86° F)
- use by expiration date on package

INACTIVE INGREDIENT

corn starch, croscarmellose sodium,D-C yellow #10 aluminum lake, FD-C yellow#6 aluminum lake, hypromellose, methacrylic acid copolymer, microcrystalline cellulose,mineral oil, polysorbate 80, simethicone, sodium hydroxide, sodium lauryl sulfate, talc, titanium dioxide, triethyl citrate

INDICATIONS AND USAGE

Use for the temporary relief of minor aches and pains due to:

headache, colds, muscle pain, menstrual pain, toothache, minor pain of arthritis or as directed by your doctor

PURPOSE

Pain Reliever

Warnings:

Reye's syndrome: Children and teenagers who have or are recovering from chicken pox or flu-like symptoms should not use this product. When using this product, if changes in behavior with nausea and vomiting occur, consult a doctor because these symptoms could be an early sign of Reye's syndrome, a rare but serious illness.

Allergy alert: Aspirin may cause a severe allergic reaction, which may include: hives, facial swelling, shock, asthmaaa9wheezing)

Stomach bleeding warning: This product contains an NSAID, which may cause severe stomach bleeding. The chance is higher if you are age 60 or older, have had stomach ulcers or bleeding problems, take a blood thinning (anticoagulant) or steroid drug, take other drugs containing prescription or nonprescription NSAIDs (aspirin, ibuprofen, naproxen or others), have 3 or more alcoholic drinks every day while using this product, take more or for a longer time than directed.

ACTIVE INGREDIENT

In each Tablet Asprin 325 mg (NSAID*) *non-steroidal anti-inflammatory drug

HOW SUPPLIED

Product: 63739-523

NDC: 63739-523-01 30 TABLET, DELAYED RELEASE in a BLISTER PACK / 25 in a BOX, UNIT-DOSE